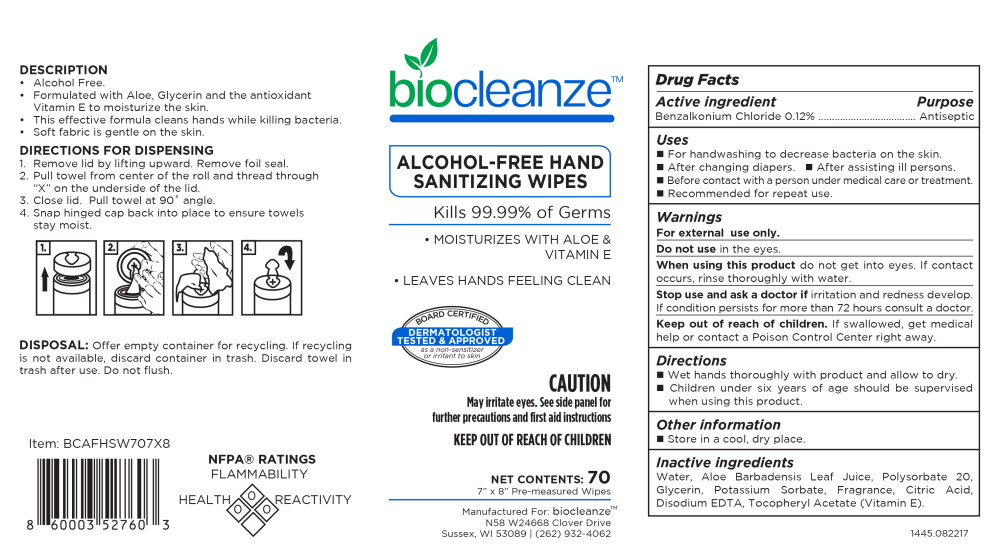 DRUG LABEL: BioCleanze
NDC: 80537-907 | Form: CLOTH
Manufacturer: Medredi LLC
Category: otc | Type: HUMAN OTC DRUG LABEL
Date: 20200908

ACTIVE INGREDIENTS: Benzalkonium Chloride 4.9 mg/1 1
INACTIVE INGREDIENTS: Water; Aloe Vera Leaf; Polysorbate 20; Glycerin; Potassium Sorbate; Citric Acid Monohydrate; Edetate Disodium; .Alpha.-Tocopherol Acetate

Drug Facts

Active ingredient

Benzalkonium Chloride 0.12%

Purpose

Antiseptic

Uses

- For handwashing to decrease bacteria on the skin.
- After changing diapers.
- After assisting ill person s.
- Before contact with a person under medical care or treatment.
- Recommended for repeat use.

Warnings

For external use only.

Do not use in the eyes.

When using this product do not get into eyes. If contact occurs, rinse thoroughly with water.

Stop use and ask a doctor if irritation and redness develop.

If condition persists for more than 72 hours consult a doctor.

Keep out of reach of children. If swallowed, get medical help or contact a Poison Control Center right away.

Directions

- Wet hands thoroughly with product and allow to dry.
- Children under six years of age should be supervised when using this product.

Other information

- Store in a cool, dry place.

Inactive ingredients

Water, Aloe Barbadensis Leaf Juice, Polysorbate 20, Glycerin, Potassium Sorbate, Fragrance, Citric Acid, Disodium EDTA, Tocopheryl Acetate (Vitamin E).

Principal Display Panel – Canister Label

biocleanze™

ALCOHOL-FREE HAND
SANITIZING WIPES

Kills 99.99% of Germs

- MOISTURIZES WITH ALOE &
  VITAMINE E
- LEAVES HANDS FEELING CLEAN

BOARD CERTIFIED

DERMATOLOGIST
TESTED & APPROVED

as a non-sensitizer
or irritant to skin

CAUTION

May irritate eyes. See side panel for
further precautions and first aid instructions

KEEP OUT OF REACH OF CHILDREN

NET CONTENTS: 70

7” x 8” Pre-measured Wipes

Manufactured For: biocleanze™

N58 W24668 Clover Drive

Sussex, WI 53089 | (262) 932-4062